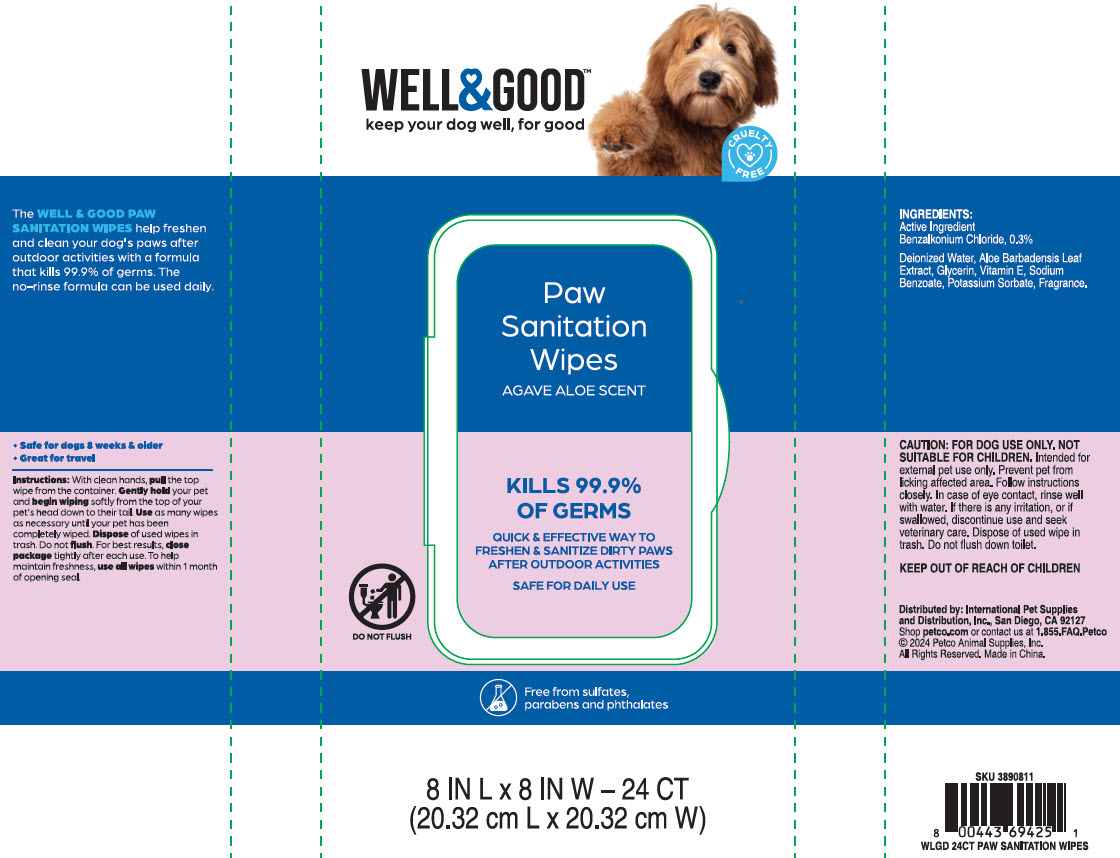 DRUG LABEL: Well and Good
NDC: 27102-522 | Form: CLOTH
Manufacturer: International Pet Supplies & Distrubtion
Category: animal | Type: OTC ANIMAL DRUG LABEL
Date: 20240821

ACTIVE INGREDIENTS: BENZALKONIUM CHLORIDE .3 g/24 1

Paw Sanitation Wipes

Caution

FOR DOG USE ONLY. NOT SUITABLE FOR CHILDREN. Intended for external pet use only. Prevent pet from licking affected area. Follow instructions closely. In case of eye contact, rinse well with water. If there is any irritation, or if swallowed, discontinue use and seek veterinary care. Dispose of used wipe in trash. Do not flush down toilet.
KEEP OUT OF REACH OF CHILDREN.

Instructions

With clean hands, pull the top wipe from container. Gently hold your pet and begin wiping softly from the top of your pet's head down to their tail. Use as many wipes as necessary until your pet has been completely wiped. Dispose of used wipes in trash. Do not flush. For best results, close package tightly after each use. To help maintain freshness, use all wipes within 1 month of opening seal.